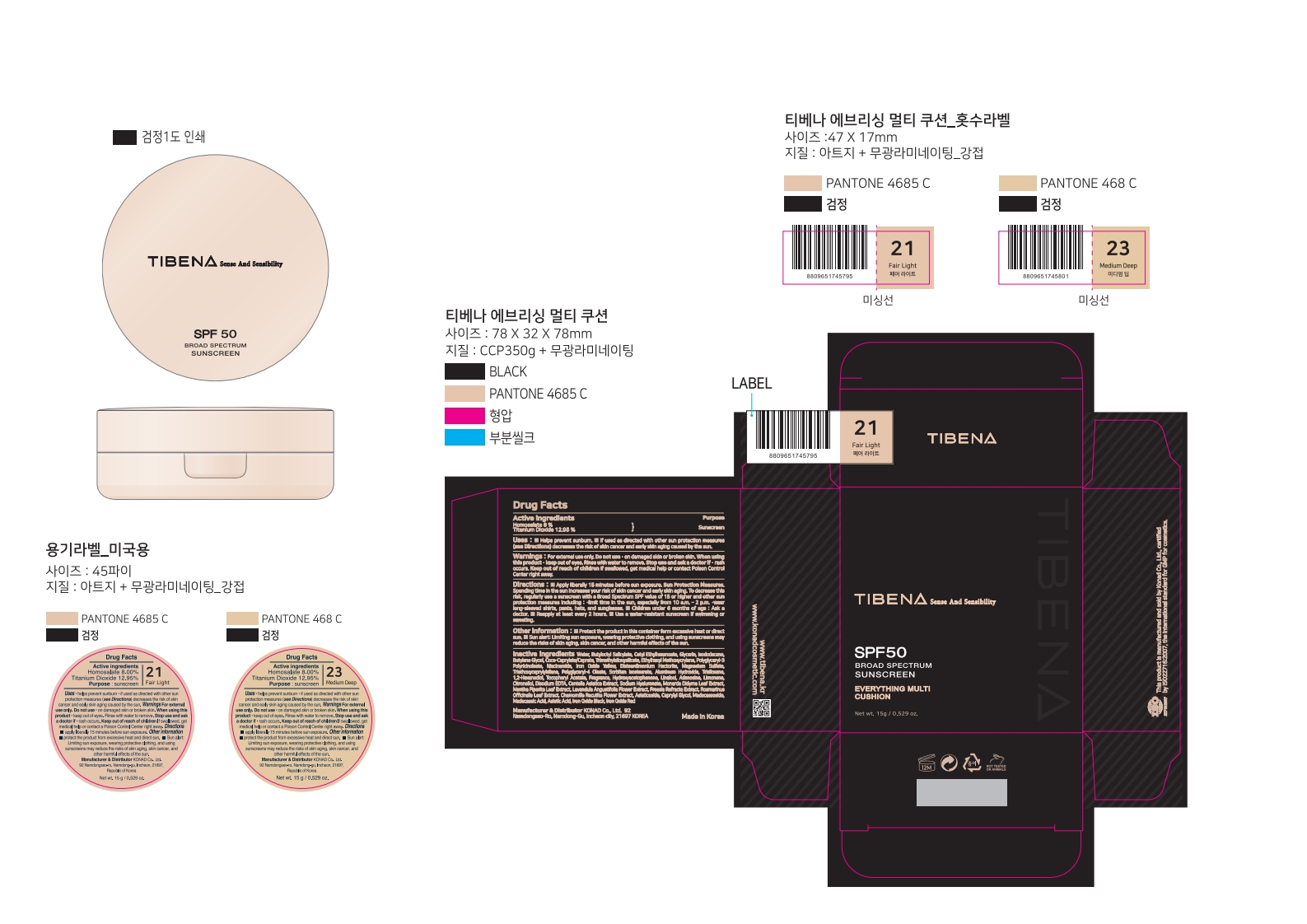 DRUG LABEL: TIBENA EVERYTHING MULTI CUSHION SPF50
NDC: 74740-715 | Form: LOTION
Manufacturer: KONAD CO LTD
Category: otc | Type: HUMAN OTC DRUG LABEL
Date: 20251027

ACTIVE INGREDIENTS: TITANIUM DIOXIDE 1.943 g/15 g; HOMOSALATE 1.2 g/15 g
INACTIVE INGREDIENTS: DISTEARDIMONIUM HECTORITE; ASIATICOSIDE; MADECASSIC ACID; ASIATIC ACID; ADENOSINE; EDETATE DISODIUM ANHYDROUS; BUTYLOCTYL SALICYLATE; NIACINAMIDE; WATER; TRIETHOXYCAPRYLYLSILANE; FERRIC OXIDE RED; ALPHA-TOCOPHEROL ACETATE; CAPRYLYL GLYCOL; FERROSOFERRIC OXIDE; CENTELLA ASIATICA TRITERPENOIDS; BUTYLENE GLYCOL; SORBITAN ISOSTEARATE; GLYCERIN; ISODODECANE; FERRIC OXIDE YELLOW; MAGNESIUM SULFATE; .BETA.-CITRONELLOL, (R)-; MADECASSOSIDE; LIMONENE, (+)-; HYALURONATE SODIUM; LINALOOL, (+/-)-; ALUMINUM HYDROXIDE; TRISILOXANE; 1,2-HEXANEDIOL; CETYL ETHYLHEXANOATE; ETHYLHEXYL METHOXYCRYLENE; COCOYL CAPRYLOCAPRATE; POLYGLYCERYL-4 OLEATE; HYDROXYACETOPHENONE; MONARDA DIDYMA LEAF; ROSEMARY

TIBENA EVERYTHING MULTI CUSHION SPF50

Active ingredients

Homosalate 8 %

Titanium Dioxide 12.95 %

Purpose

sunscreen

Uses

• helps prevent sunburn

• if used as directed with other sun protection measures (see Directions) decreases the risk of skin cancer and early skin aging caused by the sun.

Warnings

For external use only

Do not use

· on damaged skin or broken skin.

When using this product

· keep out of eyes. Rinse with water to remove.

Stop use and ask a doctor if

· rash occurs.

Keep out of reach of children

If swallowed, get medical help or contact Poison Control Center right away.

Directions

■ Apply liberally 15 minutes before sun exposure.
Sun Protection Measures.Spending time in the sun increases your risk of skin cancer and early skin aging. To decrease this risk, regularly use a sunscreen with a Broad Spectrum SPF value of 15 or higher and other sun protection measures including:
·limit time in the sun, especially from 10 a.m. – 2 p.m.
·wear long-sleeved shirts, pants, hats, and sunglasses
■ Children under 6 months of age: Ask a doctor
■ Reapply at least every 2 hours.
■ Use a water-resistant sunscreen if swimming or sweating.

Other information

■ Protect the product in this container form excessive heat or direct sun. ■ Sun alert: Limiting sun exposure, wearing protective clothing, and using sunscreens may reduce the risks of skin aging, skin cancer, and other harmful effects of the sun.

Inactive ingredients

Water, Butyloctyl Salicylate, Cetyl Ethylhexanoate, Glycerin, Isododecane, Butylene Glycol, Coco-Caprylate/Caprate, Trimethylsiloxysilicate, Ethylhexyl Methoxycrylene, Polyglyceryl-3 Polyricinoleate, Niacinamide, Iron Oxide Yellow, Disteardimonium Hectorite, Magnesium Sulfate, Triethoxycaprylylsilane, Polyglyceryl-4 Oleate, Sorbitan Isostearate, Aluminum Hydroxide, Trisiloxane, 1,2-Hexanediol, Tocopheryl Acetate, Fragrance, Hydroxyacetophenone, Linalool, Adenosine, Limonene, Citronellol, Disodium EDTA, Centella Asiatica Extract, Sodium Hyaluronate, Monarda Didyma Leaf Extract, Rosmarinus Officinalis Leaf Extract, Chamomilla Recutita Flower Extract, Asiaticoside, Caprylyl Glycol, Madecassoside, Madecassic Acid, Asiatic Acid, Iron Oxide Black, Iron Oxide Red